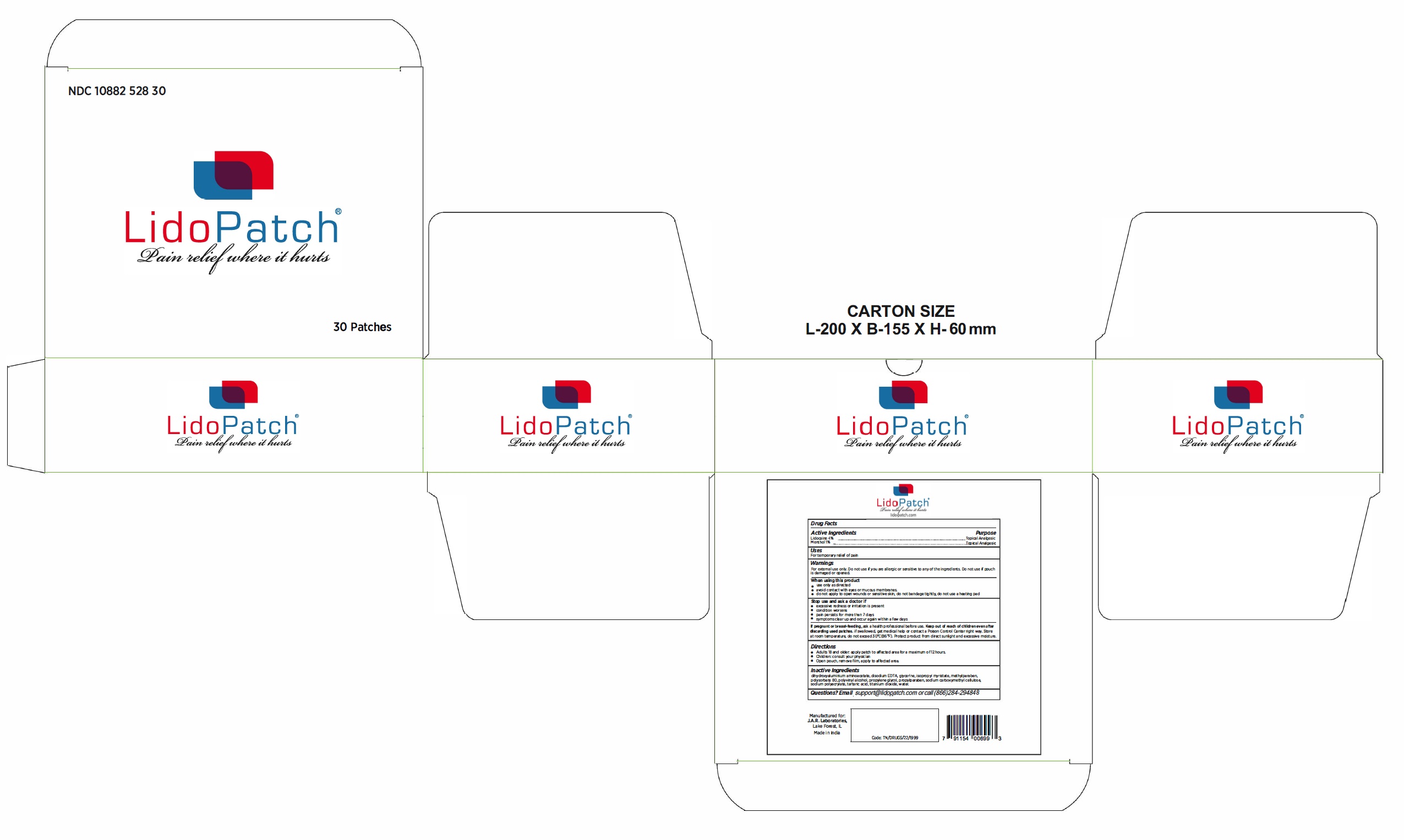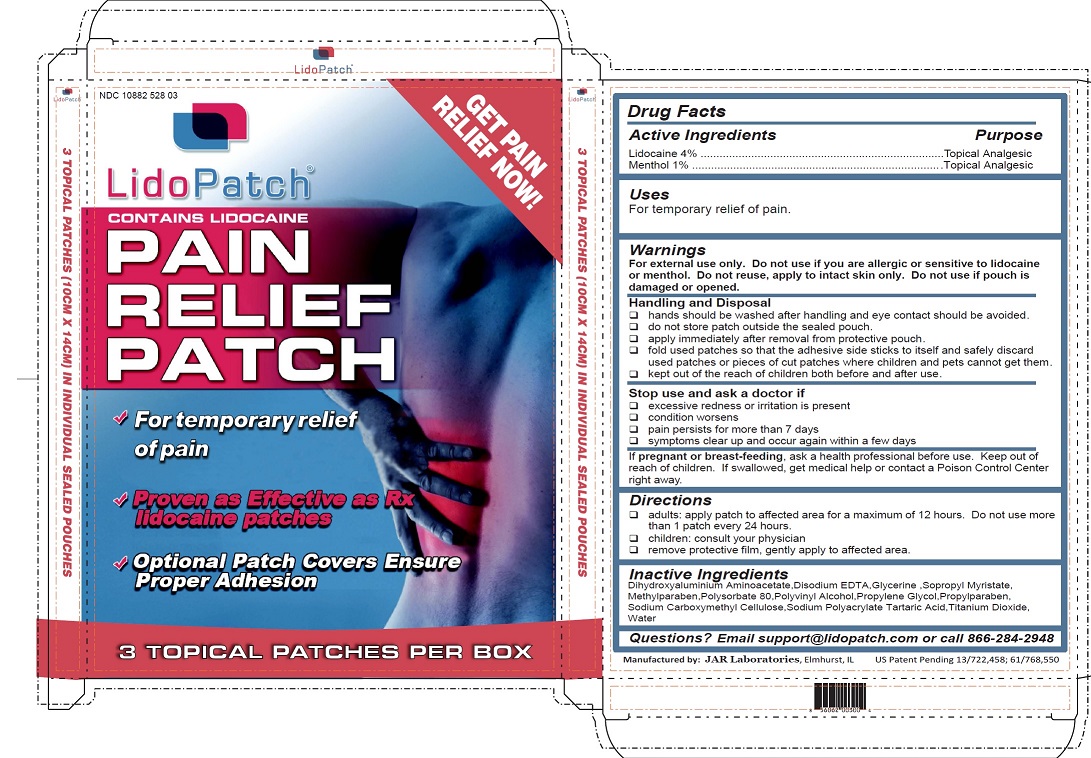 DRUG LABEL: LidoPatch Pain Relief
NDC: 10882-529 | Form: PATCH
Manufacturer: JAR Laboratories
Category: otc | Type: HUMAN OTC DRUG LABEL
Date: 20251203

ACTIVE INGREDIENTS: LIDOCAINE 100 mg/1 1; MENTHOL 400 mg/1 1
INACTIVE INGREDIENTS: PROPYLPARABEN; CARBOXYMETHYLCELLULOSE; SODIUM POLYACRYLATE (2500000 MW); TITANIUM DIOXIDE; PROPYLENE GLYCOL; POLYVINYL ALCOHOL, UNSPECIFIED; WATER; METHYLPARABEN; EDETATE DISODIUM; GLYCERIN; TARTARIC ACID; DIHYDROXYALUMINUM AMINOACETATE; POLYSORBATE 80; ISOPROPYL MYRISTATE

LidoPatch (10882-529-01, 10882-529-03, 10882-529-30)

Active Ingredients

Lidocaine 4%

Menthol 1%

Purpose

Topical Analgesic

Topical Analgesic

INDICATIONS AND USAGE

For temporary relief of pain.

Warnings

For external use only. Do not use if you are allergic or sensitive to lidocaine or menthol. Do not reuse, apply to intact skin only. Do not use if pouch is damaged or opened.

Handling and Disposal

- hands should be washed after the handling and eye contact should be avoided
- do not store patch outside the sealed pouch
- apply immediately after removal from protective pouch
- fold used patches so that the adhesive side sticks to itself and safely discard used patches or pieces of cut patches where children and pets cannot get them
- kept out of the reach of children both before and after use

Stop use and ask a doctor if

- excessive redness or irritation is present
- condition worsens
- pain persists for more than 7 days
- symptoms clear up and occur again within a few days

If pregnant or breast-feeding, ask a health professional before use.

Directions

- adults: apply patch to affected area for a maximum of 12 hours. Do not use more than 1 patch every 24 hours.
- children: consult your physician
- remove protective film, gently apply to affected area

Keep out of reach of children. If swallowed, get medical help or contact a Poison Control Center right away.

Inactive Ingredients

Dihydroxyaluminium Aminoacetate,Disodium EDTA,Glycerine ,Sopropyl Myristate, Methylparaben,Polysorbate 80,Polyvinyl Alcohol,Propylene Glycol,Propylparaben, Sodium Carboxymethyl Cellulose,Sodium Polyacrylate Tartaric Acid,Titanium Dioxide,
Water

OTHER SAFETY INFORMATION

Questions? Email support@lidopatch.com or call 866-284-2948

PACKAGE LABEL

3ct box

outer box label